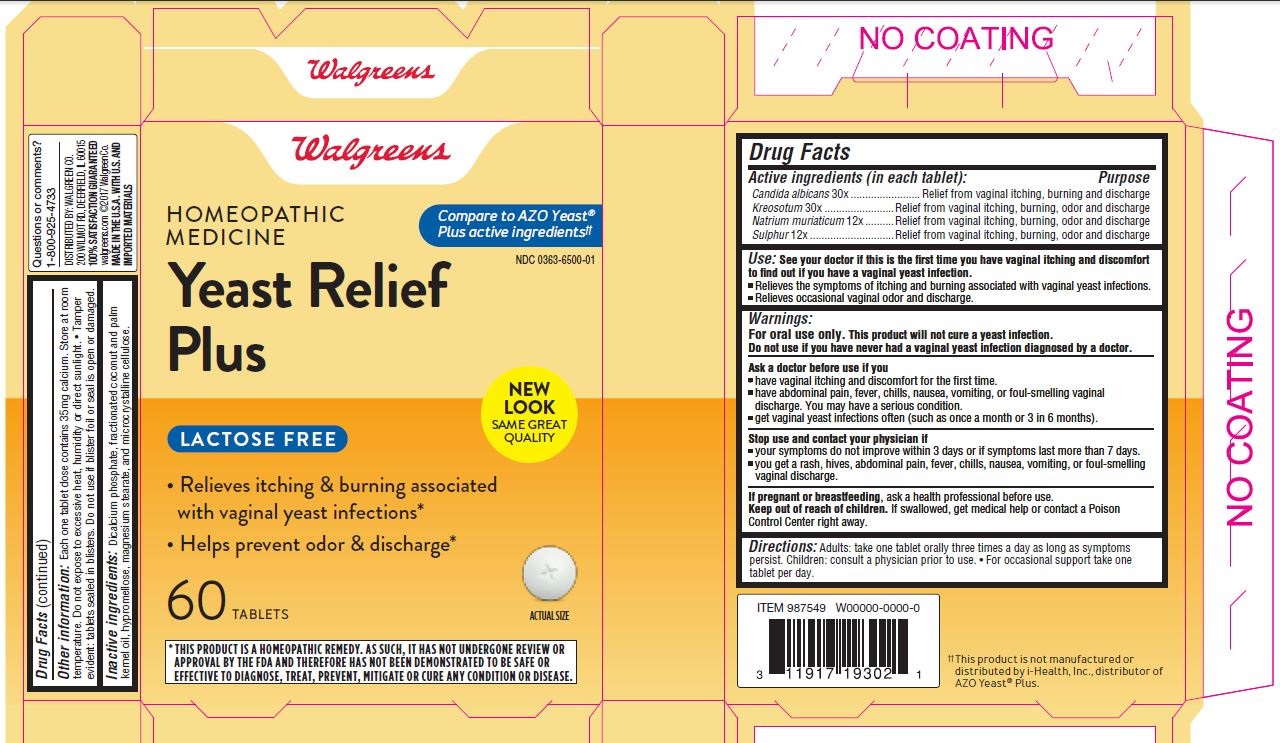 DRUG LABEL: Homeopathic Medicine Yeast Relief Plus
NDC: 0363-6500 | Form: TABLET
Manufacturer: WALGREEN CO.
Category: homeopathic | Type: HUMAN OTC DRUG LABEL
Date: 20211130

ACTIVE INGREDIENTS: CANDIDA ALBICANS 30 [hp_X]/1 g; WOOD CREOSOTE 30 [hp_X]/1 g; SODIUM CHLORIDE 12 [hp_X]/1 g; SULFUR 12 [hp_X]/1 g
INACTIVE INGREDIENTS: CALCIUM PHOSPHATE, DIBASIC, DIHYDRATE; CELLULOSE, MICROCRYSTALLINE; MAGNESIUM STEARATE; HYPROMELLOSES; MEDIUM-CHAIN TRIGLYCERIDES

Homeopathic Medicine Yeast Relief Plus

Active Ingredients (in each tablet):

Candida albicans 30X

Kreosotum 30X

Natrium muriaticum 12X

Sulphur 12X

Purpose

Relief from vaginal itching, burning and discharge

Relief from vaginal itching, burning, odor and discharge

Relief from vaginal itching, burning, odor and discharge

Relief from vaginal itching, burning, odor and discharge

Use:

See your doctor if this is the first time you have vaginal itching and discomfort to find out if you have a vaginal yeast infection.

- Relieves the symptoms of itching and burning associated with vaginal yeast infections.
- Relieves occasional vaginal odor and discharge.

Warnings:

For oral use only. This product will not cure a yeast infection.

Do not use if you have never had a vaginal yeast infection diagnosed by a doctor.

Ask a doctor before use if you

- have vaginal itching and discomfort for the first time.
- have abdominal pain, fever, chills, nausea, vomiting, or foul-smelling vaginal discharge. You may have a serious condition.
- get vaginal yeast infections often (such as once a month or three in six months).
- may have been exposed to human immunodeficiency virus (HIV) that causes AIDS.

Stop use and contact your physician if

- your symptoms do not improve within 3 days or if symptoms last more than 7 days.
- you get a rash, hives, abdominal pain, fever, chills, nausea, vomiting, or foul-smelling vaginal discharge.

PREGNANCY OR BREAST FEEDING

If pregnant or breastfeeding, ask a health professional before use.

Keep out of reach of children.

If swallowed, get medical help or contact a Poison Control Center right away.

DOSAGE AND ADMINISTRATION

Directions: Adults: take one tablet orally three times a day as long as symptoms persist. Children: consult a physician prior to use.

- For occasional support take one tablet per day.

OtherInformation:

Each one tablet dose contains 35 mg calcium. Store at room temperature. Do not expose to excessive heat, humidity or direct sunlight.

- Tamper evident: tablets sealed in blisters. Do not use if blister foil or seal is open or damaged.

Inactive Ingredients:

Dicalcium phosphate, fractionated cocunut and palm kernel oil, hypromellose, magnesium stearate, and microcrystalline cellulose.

GENERAL PRECAUTIONS

This is a homeopathic medicine that supports the body's own defense system. Because this product contains natural ingredients, color may vary.